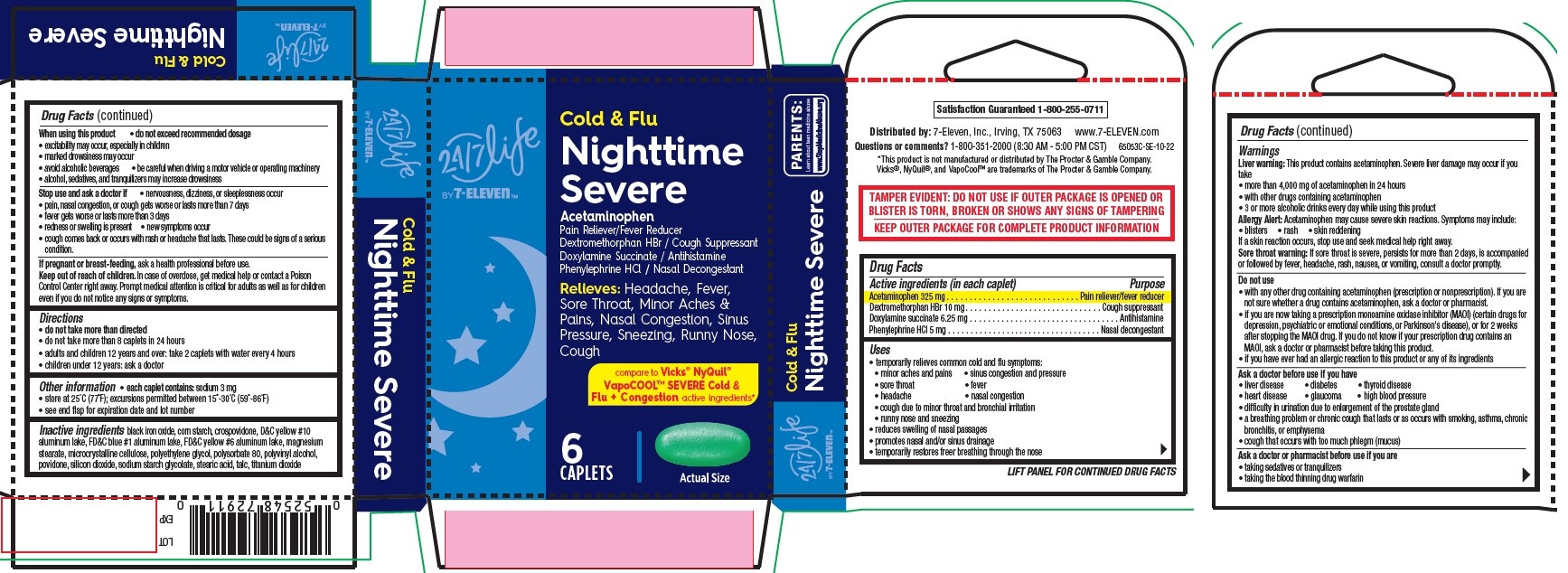 DRUG LABEL: Nighttime Severe, Cold and Flu, 24-7 Life by 7-Eleven
NDC: 66715-6505 | Form: TABLET, FILM COATED
Manufacturer: Lil' Drug Store Products, Inc.
Category: otc | Type: HUMAN OTC DRUG LABEL
Date: 20251202

ACTIVE INGREDIENTS: DEXTROMETHORPHAN HYDROBROMIDE 10 mg/1 1; ACETAMINOPHEN 325 mg/1 1; PHENYLEPHRINE HYDROCHLORIDE 5 mg/1 1; DOXYLAMINE SUCCINATE 6.25 mg/1 1
INACTIVE INGREDIENTS: SILICON DIOXIDE; TITANIUM DIOXIDE; POLYETHYLENE GLYCOL, UNSPECIFIED; MAGNESIUM STEARATE; SODIUM STARCH GLYCOLATE TYPE A POTATO; MICROCRYSTALLINE CELLULOSE; ALUMINUM OXIDE; D&C YELLOW NO. 10 ALUMINUM LAKE; STEARIC ACID; TALC; FD&C BLUE NO. 1 ALUMINUM LAKE; FD&C YELLOW NO. 6; CROSPOVIDONE; POVIDONE, UNSPECIFIED; FERROSOFERRIC OXIDE; STARCH, CORN; POLYSORBATE 80; POLYVINYL ALCOHOL, UNSPECIFIED

Nighttime Severe, Cold & Flu - 24/7 Life by 7-ElevenTM

Drug Facts

Active ingredients

Active ingredients (in each caplet)

Acetaminophen 325

Dextromethorphan HBr 10 mg

Doxylamine succinate 6.25 mg

Doxylamine succinate 6.25 mg

Purpose

Pain reliever/fever reducer

Cough suppressant

Antihistamine

Nasal decongestant

Uses

- temporarily relieves common cold and flu symptoms:
- minor aches and pains
- sinus congestion and pressure
- sore throat
- fever
- headache
- nasal congestion
- cough due to minor throat and bronchial irritation
- runny nose and sneezing
- reduces swelling of nasal passages
- promotes nasal and/or sinus drainage
- temporarily restores freer breathing through the nose

Warnings

Liver warning

Liver warning: This product contains acetaminophen. Severe liver damage may occur if you take

- more than 4,000 mg of acetaminophen in 24 hours
- with other drugs containing acetaminophen
- 3 or more alcoholic drinks every day while using this product

Allergy Alert

Allergy Alert: Acetaminophen may cause severe skin reactions. Symptoms may include:

- blisters
- rash
- skin reddening

If a skin reaction occurs, stop use and seek medical help right away.

Sore throat warning: If sore throat is severe, persists for more than 2 days, is accompanied or followed by fever, headache, rash, nausea, or vomiting, consult a doctor promptly.

Do not use

- with any other drug containing acetaminophen (prescription or nonprescription). If you are not sure whether a drug contains acetaminophen, ask a doctor or pharmacist.
- if you are now taking a prescription monoamine oxidase inhibitor (MAOI) (certain drugs for depression, psychiatric or emotional conditions, or Parkinson's disease), or for 2 weeks after stopping the MAOI drug. If you do not know if your prescription drug contains an MAOI, ask a doctor or pharmacist before taking this product.
- if you have ever had an allergic reaction to this product or any of its ingredients

Ask a doctor before use if you have

- liver disease
- diabetes
- thyroid disease
- heart disease
- glaucoma
- high blood pressure
- difficulty in urination due to enlargement of the prostate gland
- a breathing problem or chronic cough that lasts or as occurs with smoking, asthma, chronic bronchitis, or emphysema
- cough that occurs with too much phlegm (mucus)

Ask a doctor or pharmacist before use if you are

- taking sedatives or tranquilizers
- taking the blood thinning drug warfarin

When using this product

- do not exceed recommended dosage
- excitability may occur, especially in children
- marked drowsiness may occur
- avoid alcoholic beverages • be careful when driving a motor vehicle or operating machinery
- alcohol, sedatives, and tranquilizers may increase drowsiness

Stop use and ask a doctor if

- nervousness, dizziness, or sleeplessness occur
- pain, nasal congestion, or cough gets worse or lasts more than 7 days
- fever gets worse or lasts more than 3 days
- redness or swelling is present
- new symptoms occur
- cough comes back or occurs with rash or headache that lasts. These could be signs of a serious condition.

If pregnant or breast-feeding, ask a health professional before use.

Keep out of reach of children. In case of overdose, get medical help or contact a Poison Control Center right away. Prompt medical attention is critical for adults as well as for children even if you do not notice any signs or symptoms.

Directions

- do not take more than directed
- do not take more than 8 caplets in 24 hours
- adults and children 12 years and over: take 2 caplets with water every 4 hours
- children under 12 years: ask a doctor

Other information

- each caplet contains: sodium 3 mg
- store at 25°C (77°F); excursions permitted between 15°-30°C (59°-86°F)
- see end flap for expiration date and lot number

Inactive ingredients

black iron oxide, corn starch, crospovidone, D&C yellow #10 aluminum lake, FD&C blue #1 aluminum lake, FD&C yellow #6 aluminum lake, magnesium stearate, microcrystalline cellulose, polyethylene glycol, polysorbate 80, polyvinyl alcohol, povidone, silicon dioxide, sodium starch glycolate, stearic acid, talc, titanium dioxide

Nighttime Severe, Cold & Flu - 24/7 Life by 7-ElevenTM

[24/7 Life by 7-ElevenTM logo]

Cold & Flu
Nighttime
Severe

Acetaminophen

Pain Reliever/Fever Reducer
Dextromethorphan HBr / Cough Suppressant
Doxylamine Succinate / Antihistamine
Phenylephrine HCl / Nasal Decongestant
Relieves: Headache, Fever,
Sore Throat, Minor Aches &
Pains, Nasal Congestion, Sinus
Pressure, Sneezing, Runny Nose,
Cough

compare to Vicks® NyQuil®
VapoCOOL™ SEVERE Cold &
Flu + Congestion active ingredients*

6

CAPLETS

[caplet image]

Actual Size